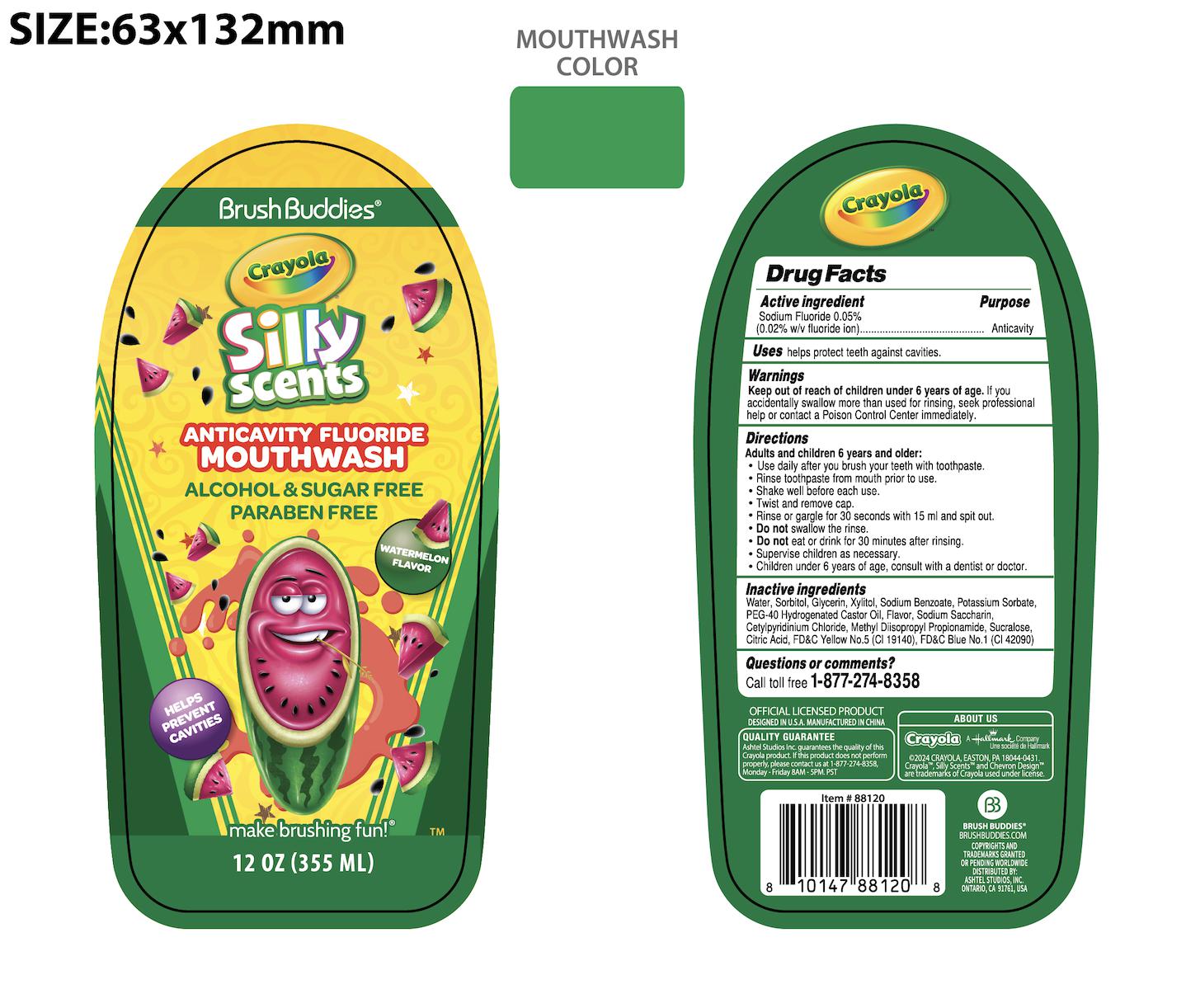 DRUG LABEL: BRUSH BUDDIES CRAYOLA ANTICAVITY FLUORIDE WATERMELON
NDC: 73928-036 | Form: LIQUID
Manufacturer: Kingkey MBC Life Technology Group Co.,Ltd
Category: otc | Type: HUMAN OTC DRUG LABEL
Date: 20251211

ACTIVE INGREDIENTS: SODIUM FLUORIDE 0.05 g/100 mL
INACTIVE INGREDIENTS: SORBITOL; SODIUM BENZOATE; POLYOXYL 40 HYDROGENATED CASTOR OIL; FD&C YELLOW NO. 5; POTASSIUM SORBATE; CETYLPYRIDINIUM CHLORIDE; METHYL DIISOPROPYL PROPIONAMIDE; CITRIC ACID MONOHYDRATE; WATER; XYLITOL; FD&C BLUE NO. 1; SUCRALOSE; GLYCERIN

BRUSH BUDDIES CRAYOLA ANTICAVITY FLUORIDE WATERMELON 73928-036 (0.05%)

Active ingredient

SODIUM FLUORIDE 0.05%

Puropse

(0.05% w/v fluoride ion)---------Anticavity

Uses

helps protect teeth against cavities.

Warnings

Keep out of reach of children under 6 years of age.If you accidentally swallow more than used for rinsing, seek professional help or contact a Poison Control Center immediately.

Directions

Adults and children 6 years and older:

- Use daily after you brush your teeth with toothpaste.
- Rinse toothpaste from mouth prior to use.
- Shake well before each use.
- Twist and remove cap.
- Rinse or gargle for 30 seconds with 15 ml and spit out
- Do Not swallow the rinse.
- Do Not eat or drink for 30 minutes after rinsing.
- Supervise children as necessary.
- Children under 6 years of age, consult with a dentist or doctor

Inactive ingredients

WATER
SORBITOL
GLYCERIN
XYLITOL
POTASSIUM SORBATE
SODIUM BENZOATE
PEG-40 HYDROGENATED CASTOR OIL
FLAVOR
SODIUM SACCHARIN
CETYLPYRIDINIUM CHLORIDE

METHYL DIISOPROPYL PROPIONAMIDE

SUCRALOSE
CITRIC ACID

FD&C Yellow No.5（CI 19140）

FD&C Blue No.1（CI 42090）

Questions or comments?

Call toll free 1-877-274-8358